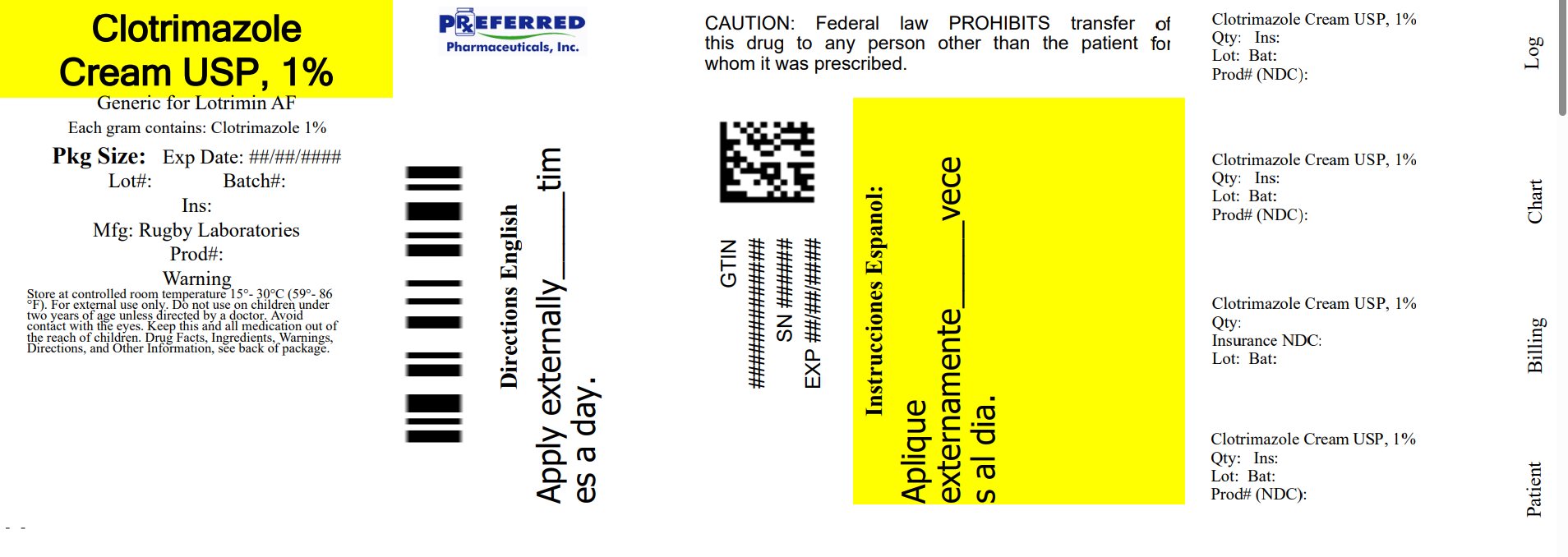 DRUG LABEL: Rugby Clotrimazole Antifungal Cream
NDC: 68788-8901 | Form: CREAM
Manufacturer: Preferred Pharmaceuticals Inc.
Category: otc | Type: HUMAN OTC DRUG LABEL
Date: 20250725

ACTIVE INGREDIENTS: CLOTRIMAZOLE 1 g/100 g
INACTIVE INGREDIENTS: DIMETHYL SULFOXIDE; ETHYLPARABEN; GLYCERIN; GLYCERYL STEARATE SE; LAURETH-23; LIGHT MINERAL OIL; PETROLATUM; STEARYL ALCOHOL; WATER

Clotrimazole cream USP, 1%

Active ingredient

Clotrimazole USP 1% w/w

Purpose

Antifungal Cream

KEEP OUT OF REACH OF CHILDREN

Keep this and all drugs out of the reach of children. In case of accidental ingestion, seek professional assistance or contact a Poison Control Center right away.

Uses

Cures athlete’s foot (tinea pedis), jock itch (tinea cruris), ringworm (tinea corporis). Relieves the itching, irritation, redness, scaling and discomfort which can accompany these conditions.

Warnings

● For external use only

● Do not use on children under 2 years of age unless directed by a doctor.

● Avoid contact with eyes.

Directions

- Wash the affected area and dry thoroughly.

● Apply a thin layer of this product over affected area twice daily (morning and night), or as directed by a doctor.

● Supervise children in the use of this product.

● For athlete’s foot, pay special attention to the spaces between the toes; wear well-fitting ventilated shoes, and change shoes and socks at least once daily.

● For athlete’s foot and ringworm, use daily for 4 weeks. For jock itch, use daily for 2 weeks.

● If conditions persists longer, consult a doctor.

● This product is not effective on the scalp or nails.

Stop Use and ask a doctor if

- Irritation occurs
- There is no improvement within 4 weeks (for athlete's foot or ringworm) or within 2 weeks (for jock itch).

Inactive Ingredients

Dimethyl Sulfoxide, Ethylparaben, Glycerin, Glyceryl Stearate SE, Laureth-23, Light Mineral Oil, Petrolatum, Stearyl Alcohol, Water

Other Information

- store at controlled room temperature 15°-30°C (59°- 86°F)
- Close cap tightly after use.

Other Information

Clotrimazole Antifungal Cream is not manufactured or distributed by Bayer, owners of the registered trademark Lotrimin®AF.

Questions

Keep carton for complete Drug Facts

Call 1-800-645-2158

Distributed by:

RUGBY® LABORATORIES

17177 N. Laurel Park Drive, Suite 233

Livonia, MI 48152

www.rugbylaboratories.com

Relabeled By: Preferred Pharmaceuticals Inc.

68788-8901-2

Made in China